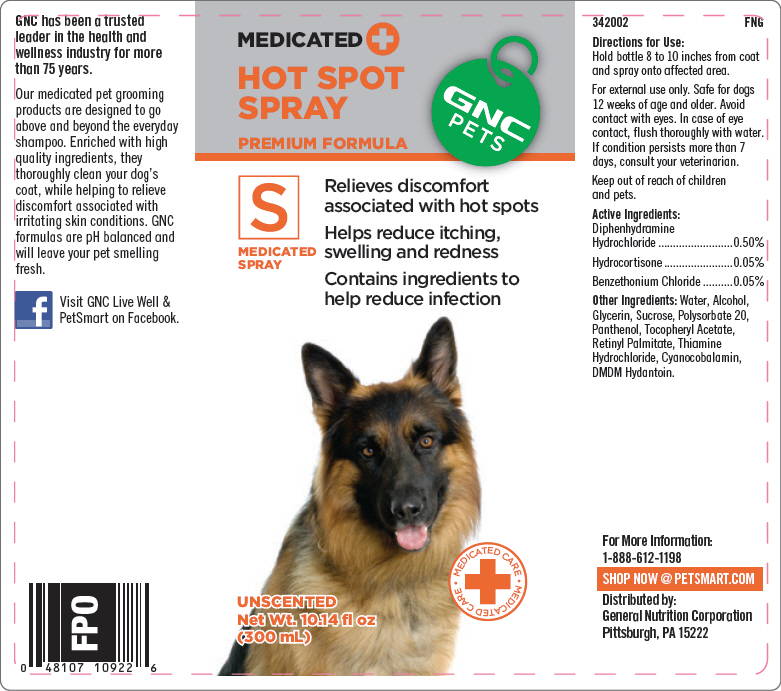 DRUG LABEL: GNC Pets Hot Spot (Premium Formula)
NDC: 43655-002 | Form: SPRAY
Manufacturer: General Nutrition Corporation
Category: animal | Type: OTC ANIMAL DRUG LABEL
Date: 20181105

ACTIVE INGREDIENTS: Diphenhydramine Hydrochloride 5 mg/1 mL; Hydrocortisone 0.5 mg/1 mL; Benzethonium Chloride 0.5 mg/1 mL
INACTIVE INGREDIENTS: Water; Alcohol; Glycerin; Sucrose; Polysorbate 20; Panthenol; .Alpha.-Tocopherol Acetate; Vitamin A Palmitate; Thiamine Hydrochloride; Cyanocobalamin; DMDM Hydantoin

GNC Pets Hot Spot Spray (Premium Formula)

342002
FNG

Directions for Use:

Hold bottle 8 to 10 inches from coat and spray onto affected area.

SAFE HANDLING WARNING

For external use only. Safe for dogs 12 weeks of age and older. Avoid contact with eyes. In case of eye contact, flush thoroughly with water. If condition persists more than 7 days, consult your veterinarian.

Keep out of reach of children and pets.

DESCRIPTION

Active Ingredients:
Diphenhydramine Hydrochloride | 0.50%
Hydrocortisone | 0.05%
Benzethonium Chloride | 0.05%

Other Ingredients: Water, Alcohol, Glycerin, Sucrose, Polysorbate 20, Panthenol, Tocopheryl Acetate, Retinyl Palmitate, Thiamine Hydrochloride, Cyanocobalamin, DMDM Hydantoin.

For More Information:

1-888-612-1198

SHOP NOW @ PETSMART.COM

Distributed by:
General Nutrition Corporation
Pittsburgh, PA 15222

PRINCIPAL DISPLAY PANEL - 300 mL Bottle Label

MEDICATED +
HOT SPOT
SPRAY

GNC
PETS

PREMIUM FORMULA

S
MEDICATED
SPRAY

Relieves discomfort
associated with hot spots

Helps reduce itching,
swelling and redness

Contains ingredients to
help reduce infection

• MEDICATED CARE
+
• MEDICATED CARE

UNSCENTED
Net Wt. 10.14 fl oz
(300 mL)